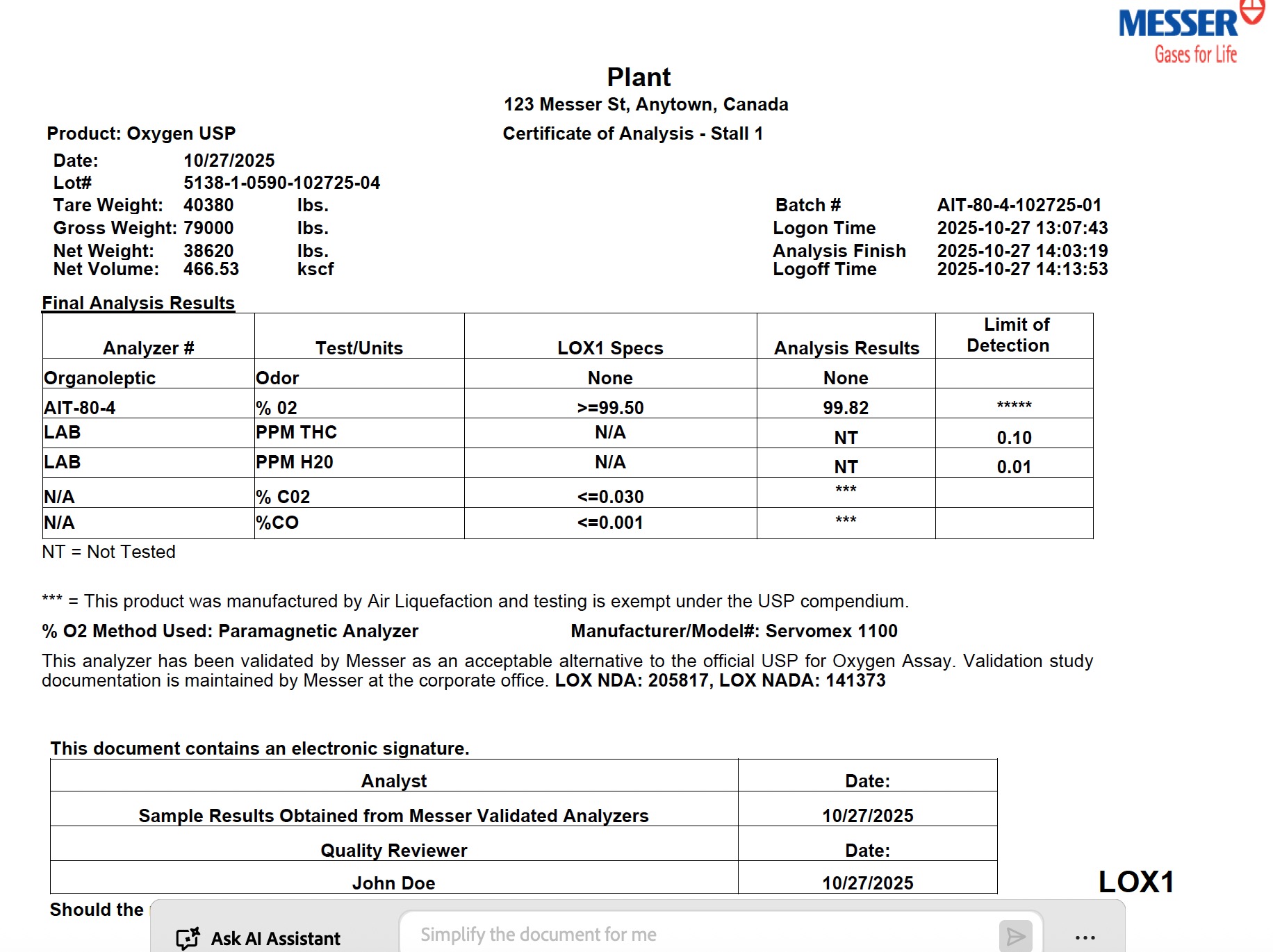 DRUG LABEL: Oxygen
NDC: 52003-911 | Form: GAS
Manufacturer: Messer Canada Inc.
Category: animal | Type: PRESCRIPTION ANIMAL DRUG LABEL
Date: 20251114

ACTIVE INGREDIENTS: OXYGEN 995 mL/1 L

Oxygen USP Bulk Liquid

PACKAGE LABEL

Plant
123 Messer St, Anytown, Canada
Certificate of Analysis - Stall 1
Product: Oxygen USP
Date: 10/27/2025
Lot#: 5138-1-0590-102725-04
Tare Weight: 40380 lbs.
Gross Weight: 79000 lbs.
Net Weight: 38620 lbs.
Net Volume: 466.53 kscf
Batch #: AIT-80-4-102725-01
Logon Time: 2025-10-27 13:07:43
Analysis Finish: 2025-10-27 14:03:19
Logoff Time: 2025-10-27 14:13:53
Final Analysis Results
Analyzer # Test/Units LOX1 Specs Analysis Results Limit of Detection
Organoleptic Odor None None
AIT-80-4 % O₂ ≥ 99.50 99.82 *****
LAB PPM THC N/A NT 0.10
LAB PPM H₂O N/A NT 0.01
N/A % CO₂ ≤ 0.030 ***
N/A % CO ≤ 0.001 ***
NT = Not Tested
*** = This product was manufactured by Air Liquefaction and testing is exempt under the USP compendium.
% O₂ Method Used: Paramagnetic Analyzer Manufacturer/Model#: Servomex 1100
This analyzer has been validated by Messer as an acceptable alternative to the official USP for Oxygen Assay. Validation study documentation is maintained by Messer at the corporate office. LOX NDA: 205817, LOX NADA: 141373
This document contains an electronic signature.
Analyst Date
Sample Results Obtained from Messer Validated Analyzers 10/27/2025
Quality Reviewer Date
John Doe 10/27/2025
Should the material not be delivered to an USP customer, the material is "Not Approved for Human Drug Use"
LOX1